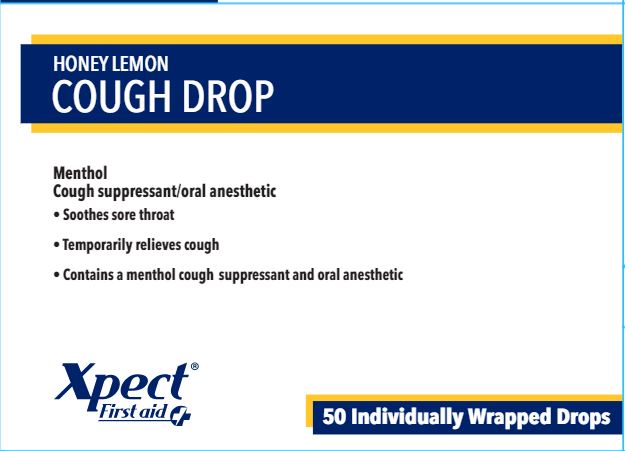 DRUG LABEL: Xpect Honey Lemon Cough Drops
NDC: 42961-233 | Form: LOZENGE
Manufacturer: Cintas Corporation
Category: otc | Type: HUMAN OTC DRUG LABEL
Date: 20250923

ACTIVE INGREDIENTS: MENTHOL 9 mg/1 1
INACTIVE INGREDIENTS: BETA CAROTENE; CORN SYRUP; EUCALYPTUS OIL; HONEY; LECITHIN, SOYBEAN; SUCROSE; WATER

Xpect Honey Lemon Cough Drop

Active ingredient (in each drop)

Menthol 9 mg

Purpose

Cough suppressant/oral anesthetic

Uses

temporarily relieves:

- cough due to a cold
- occasional minor irritation or sore throat

Warnings

Sore throat warning: Severe or persistent sore throat or sore throat accompanied by high fever, headache, rash, swelling, nausea, or vomiting may be serious. Consult a doctor promptly. Do not use more than 2 days unless directed by a doctor

Ask a doctor before use if you have

- persistent or chronic cough such as occurs with smoking, asthma, or emphysema
- cough accompanied by excessive phlegm (mucus)

Stop use and ask a doctor if

- cough persists for more than 1 week, tends to recur, or is accompanies by fever, rash, or persistent headache. These could be signs of a serious condition.
- sore mouth does not improve in 7 days
- irritation, pain, or redness persists or worsens

Keep out of reach of children.

Directions

- do not take more than directed
- adults and children 5 years and over: dissolve 1 drop slowly in the mouth. Repeat every 2 hours as needed.
- children under 5 years: ask a doctor

Other information

- 12 calories per drop
- Contains: SOY

Inactive ingredients

beta carotene (color), corn syrup, eucalyptus oil, honey, natural & artificial flavors, soy lecithin, sucrose, water

Questions or comments?

1-877-973-2811 Monday - Friday 8:00 am - 5:00 pm

Principal Display Panel - 42961-233-02

HONEY LEMON COUGH DROP

Menthol

Cough suppressant/oral anesthetic

- Soothes sore throat
- Temporarily relieves cough
- Contains a menthol cough suppressant and oral anesthetic

Xpect® First aid

50 Individually Wrapped Drops